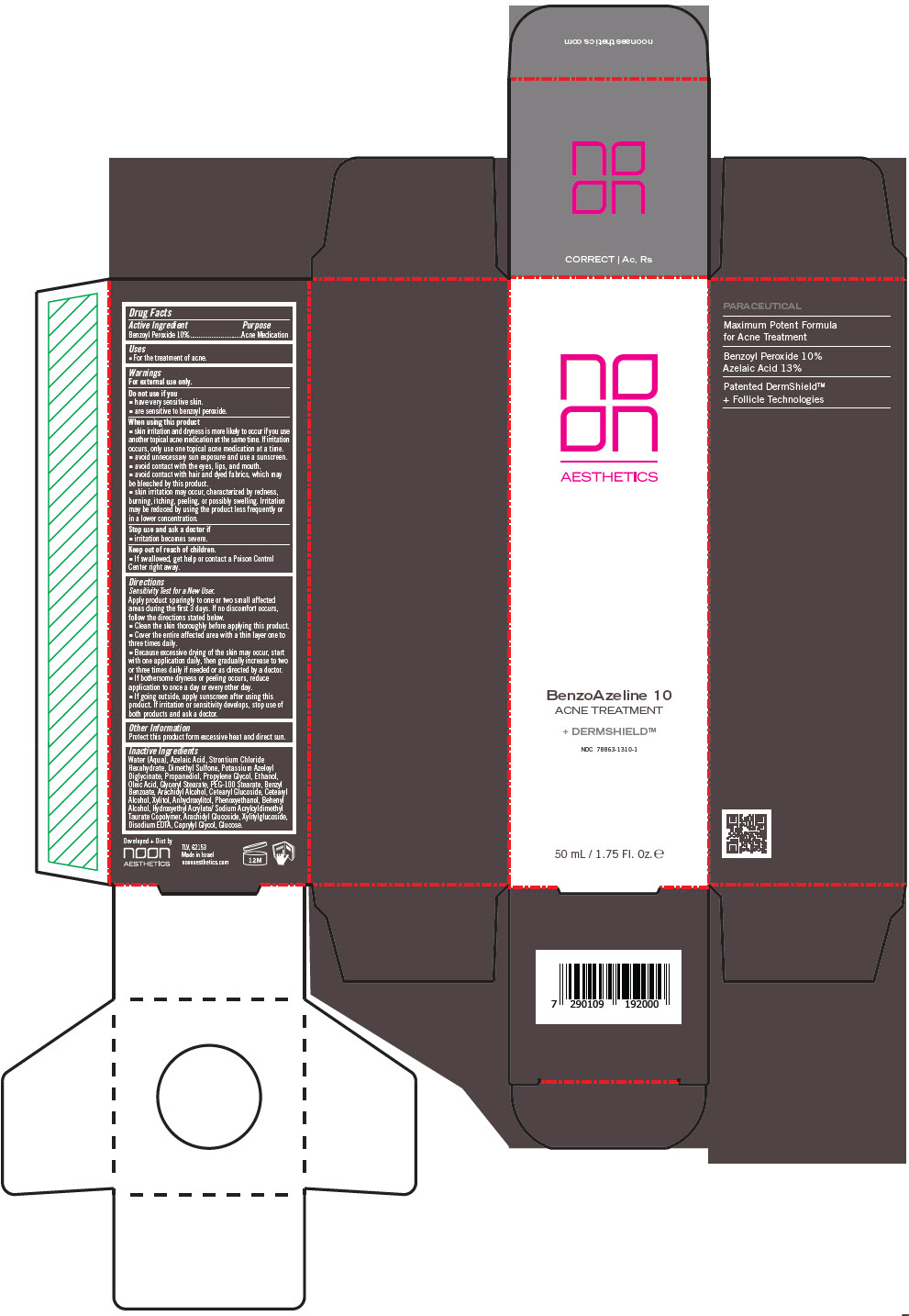 DRUG LABEL: BenzoAzeline 10
NDC: 78863-1310 | Form: CREAM
Manufacturer: Noon Aesthetics M.R. Ltd
Category: otc | Type: HUMAN OTC DRUG LABEL
Date: 20260116

ACTIVE INGREDIENTS: BENZOYL PEROXIDE 1000 mg/1 mL
INACTIVE INGREDIENTS: WATER; AZELAIC ACID; POTASSIUM AZELOYL DIGLYCINATE; DIMETHYL SULFONE; STRONTIUM CHLORIDE HEXAHYDRATE; MEDIUM-CHAIN TRIGLYCERIDES; ALCOHOL; GLYCERYL STEARATE SE; PROPANEDIOL; PROPYLENE GLYCOL; OLEIC ACID; PEG-100 MONOSTEARATE; BENZYL BENZOATE; ARACHIDYL ALCOHOL; CETEARYL GLUCOSIDE; CETOSTEARYL ALCOHOL; XYLITOL; ANHYDROXYLITOL; DOCOSANOL; HYDROXYETHYL ACRYLATE/SODIUM ACRYLOYLDIMETHYL TAURATE COPOLYMER (100000 MPA.S AT 1.5%); ARACHIDYL GLUCOSIDE; PHENOXYETHANOL; XYLITYLGLUCOSIDE; CAPRYLYL GLYCOL; DEXTROSE MONOHYDRATE; EDETATE DISODIUM ANHYDROUS

BenzoAzeline 10

Drug Facts

Active Ingredient

Benzoyl Peroxide 10%

Purpose

Acne Medication

Uses

- For the treatment of acne.

Warnings

For external use only.

Do not use if you

- have very sensitive skin.
- are sensitive to benzoyl peroxide.

When using this product

- skin irritation and dryness is more likely to occur if you use another topical acne medication at the same time. If irritation occurs, only use one topical acne medication at a time.
- avoid unnecessary sun exposure and use a sunscreen.
- avoid contact with the eyes, lips, and mouth.
- avoid contact with hair and dyed fabrics, which may be bleached by this product.
- skin irritation may occur, characterized by redness, burning, itching, peeling, or possibly swelling. Irritation may be reduced by using the product less frequently or in a lower concentration.

Stop use and ask a doctor if

- irritation becomes severe.

Keep out of reach of children.

- If swallowed, get help or contact a Poison Control Center right away.

Directions

Sensitivity Test for a New User.

Apply product sparingly to one or two small affected areas during the first 3 days. If no discomfort occurs, follow the directions stated below.

- Clean the skin thoroughly before applying this product.
- Cover the entire affected area with a thin layer one to three times daily.
- Because excessive drying of the skin may occur, start with one application daily, then gradually increase to two or three times daily if needed or as directed by a doctor.
- If bothersome dryness or peeling occurs, reduce application to once a day or every other day.
- If going outside, apply sunscreen after using this product. If irritation or sensitivity develops, stop use of both products and ask a doctor.

Other Information

Protect this product form excessive heat and direct sun.

Inactive Ingredients

Water (Aqua), Azelaic Acid, Strontium Chloride Hexahydrate, Dimethyl Sulfone, Potassium Azeloyl Diglycinate, PropanedioI, Propylene Glycol, Ethanol, Oleic Acid, Glyceryl Stearate, PEG-100 Stearate, Benzyl Benzoate, Arachidyl Alcohol, Cetearyl Glucoside, Cetearyl Alcohol, Xylitol, Anhydroxylitol, Phenoxyethanol, Behenyl Alcohol, Hydroxyethyl Acrylate/ Sodium Acryloyldimethyl Taurate Copolymer, Arachidyl Glucoside, Xylitylglucoside, Disodium EDTA, Caprylyl Glycol, Glucose.

Developed + Dist by
noon
AESTHETICS

PRINCIPAL DISPLAY PANEL - 50 mL Tube Carton

no
on
AESTHETICS

BenzoAzeline 10
ACNE TREATMENT

+ DERMSHIELD™

NDC 78863-1310-1

50 mL / 1.75 Fl. Oz. ℮